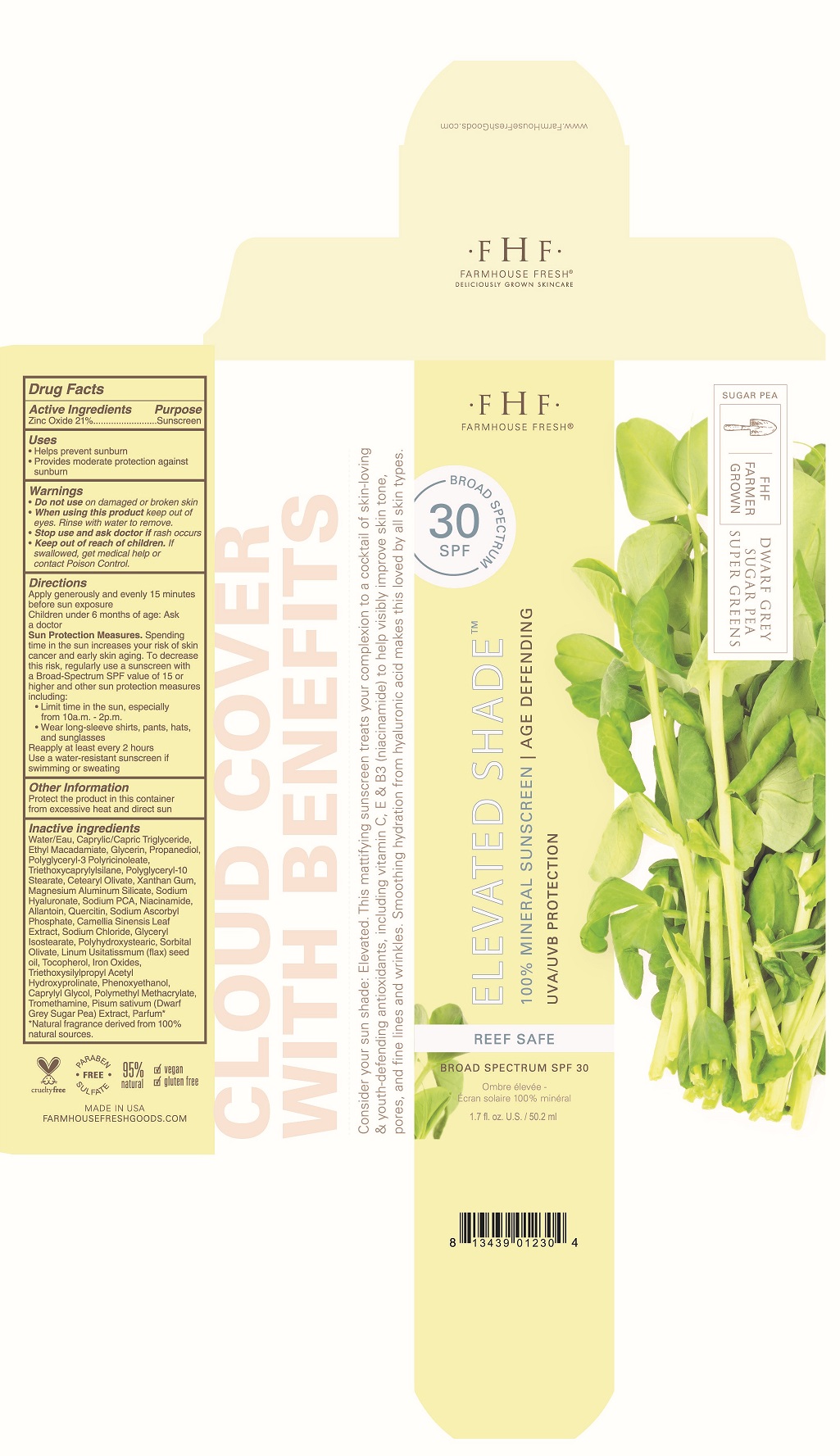 DRUG LABEL: FARMHOUSE FRESH ELEVATED SHADE
NDC: 72788-101 | Form: CREAM
Manufacturer: SUMMER SOLES LLC
Category: otc | Type: HUMAN OTC DRUG LABEL
Date: 20201228

ACTIVE INGREDIENTS: ZINC OXIDE 21 g/100 mL
INACTIVE INGREDIENTS: water; MEDIUM-CHAIN TRIGLYCERIDES; ETHYL MACADAMIATE; GLYCERIN; PROPANEDIOL; POLYGLYCERYL-3 RICINOLEATE; TRIETHOXYCAPRYLYLSILANE; POLYGLYCERYL-10 STEARATE; CETEARYL OLIVATE; XANTHAN GUM; MAGNESIUM ALUMINUM SILICATE; HYALURONATE SODIUM; SODIUM PYRROLIDONE CARBOXYLATE; NIACINAMIDE; ALLANTOIN; QUERCETIN; SODIUM ASCORBYL PHOSPHATE; GREEN TEA LEAF; SODIUM CHLORIDE; GLYCERYL ISOSTEARATE; POLYHYDROXYSTEARIC ACID (2300 MW); SORBITAN OLIVATE; FLAX SEED; TOCOPHEROL; FERRIC OXIDE RED; TRIETHOXYSILYLPROPYL STEARDIMONIUM; OXACEPROL; PHENOXYETHANOL; CAPRYLYL GLYCOL; POLY(METHYL METHACRYLATE; 450000 MW); TROMETHAMINE; PISUM SATIVUM WHOLE

FARMHOUSE FRESH ELEVATED SHADE SPF 30

ACTIVE INGREDIENTS

Zinc Oxide 21.50%

PURPOSE

SUNSCREEN

Uses

- Helps protect against sunburn
- provides moderate protection against sunburn

Warnings

- Do not use on damaged or broken skin
- When using this product keep out of eyes. Rinse with water to remove
- Stop use and ask doctor if rash occurs

Keep out of reach of children If swallowed, get medicl help or contact poison control center.

Directions

Apply generously and evenly 15 minutes before sun exposure.
Children under 6 months of age: ask doctor.
Sun protection measures. Spending time in the sun increases your risk of skin cancer and early skin aging. To decrease the risk, regularly use a sunscreen with a Broad-Spectrum SPF value of 15 or higher and other sun protection measures including:

- Limit time in the sun, especially from 10a.m. - 2p.m.
- wear long sleeve shirts, pants, hats and sunglasses.

Reapply at least every 2 hours
Use a water-resistant sunscreen if swimming or sweating

Other Information

Protect the product in this contianer from heat and direct sun.

INACTIVE INGREDIENTS

Water/Eau, Caprylic/Capric Triglyceride, Ethyl Macadamiate, Glycerin, Propanediol, Polyglyceryl-3 Polyricinoleate, Triethoxycaprylylsilane, Polyglyceryl-10 Stearate, Cetearyl Olivate, Xanthan Gum, Magnesium Aluminum Silicate, Sodium Hyaluronate, Sodium PCA, Niacinamide, Allantoin, Quercetin, Sodium Ascorbyl Phosphate, Camellia Sinensis Leaf Extract, Sodium Chloride, Glyceryl Isostearate, Polyhydroxystearic, Sorbital Olivate, Linum Usitatissmum (flax) seed oil, Tocopherol, Iron Oxides, Triethoxysilylpropyl Acetyl Hydroxyprolinate, Phenoxyethanol, Caprylyl Glycol, Polymethyl Methacrylate, Tromethamine, Pisum sativum (Dwarf Gray Sugar Pea) Extract, Parfum* *Natural fragrance derived from 100% natural sources.